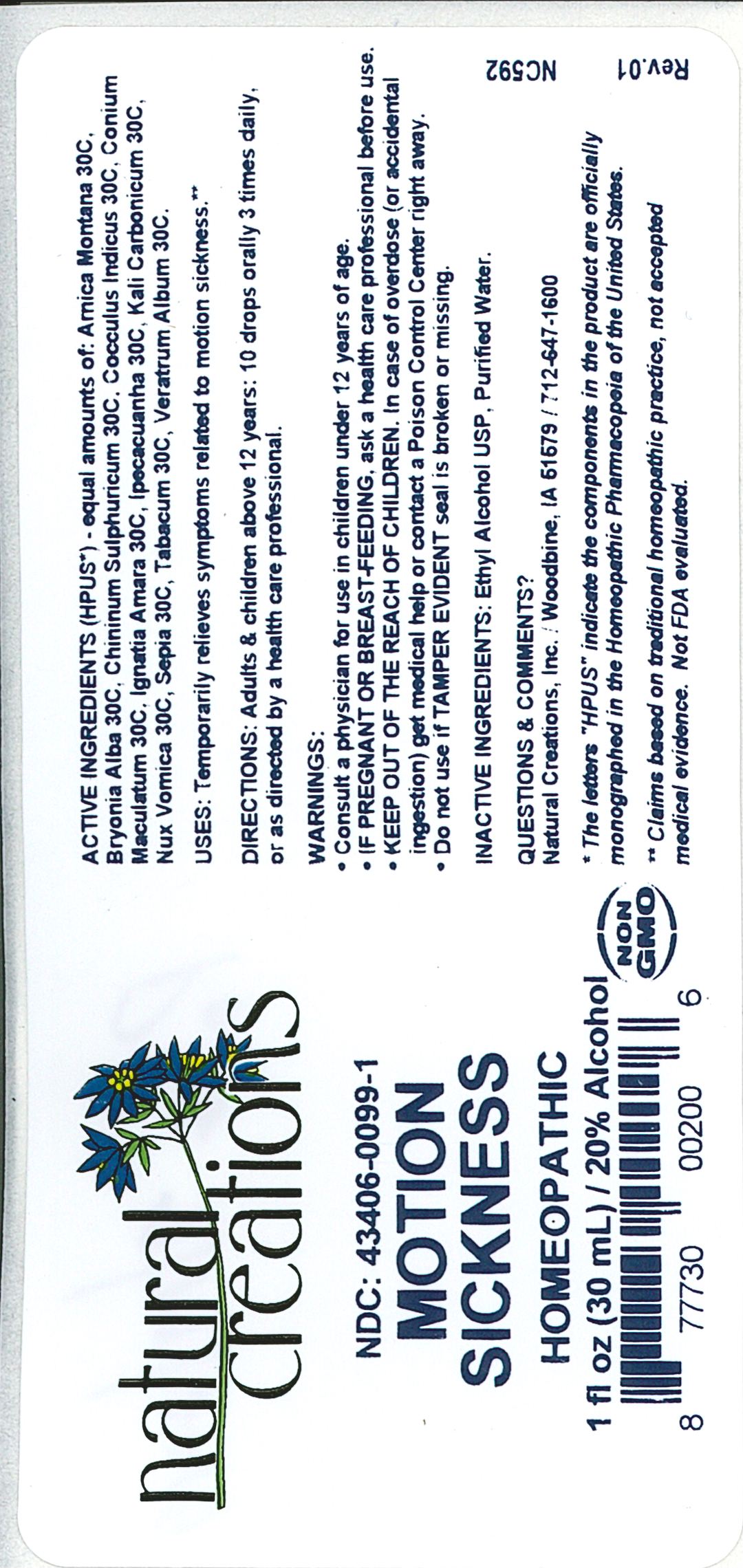 DRUG LABEL: MOTION SICKNESS HP
NDC: 43406-0099 | Form: LIQUID
Manufacturer: Natural Creations, Inc.
Category: homeopathic | Type: HUMAN OTC DRUG LABEL
Date: 20230103

ACTIVE INGREDIENTS: ARNICA MONTANA 30 [hp_C]/1 mL; BRYONIA ALBA ROOT 30 [hp_C]/1 mL; QUININE SULFATE 30 [hp_C]/1 mL; ANAMIRTA COCCULUS SEED 30 [hp_C]/1 mL; CONIUM MACULATUM FLOWERING TOP 30 [hp_C]/1 mL; STRYCHNOS IGNATII SEED 30 [hp_C]/1 mL; IPECAC 30 [hp_C]/1 mL; POTASSIUM CARBONATE 30 [hp_C]/1 mL; STRYCHNOS NUX-VOMICA SEED 30 [hp_C]/1 mL; SEPIA OFFICINALIS JUICE 30 [hp_C]/1 mL; TOBACCO LEAF 30 [hp_C]/1 mL; VERATRUM ALBUM ROOT 30 [hp_C]/1 mL
INACTIVE INGREDIENTS: WATER; ALCOHOL

MOTION SICKNESS HP

ACTIVE INGREDIENT

ACTIVE INGREDIENTS (HPUS*) - equal amounts of: Arnica Montana 30C, Bryonia Alba 30C, Chininum Sulphuricum 30C, Cocculus Indicus 30C, Conium Maculatum 30C, Ignatia Amara 30C, Ipecacuanha 30C, Kali Carbonicum 30C, Nux Vomica 30C, Sepia 30C, Tabacum 30C, Veratrum Album 30C

INDICATIONS AND USAGE

USES: Temporarily relieves symptoms related to motion sickness.**

WARNING:

- Consult a physician for use in children under 12 years of age.
- IF PREGNANT OR BREAST-FEEDING, ask a health care professional before use.
- KEEP OUT OF THE REACH OF CHILDREN. In case of overdose (or accidental ingestion) get medical help or contact a Poison Control Center right away.
- Do not use it TAMPER EVIDENT seal is broken or missing.

DOSAGE AND ADMINISTRATION

DIRECTIONS: Adults and children above 12 years: 10 drops orally 3 times daily, or as directed by a health care professional.

REFERENCES

*The letters "HPUS" indicate the components in the product are officially monographed in the Homeopathic Pharmacopeia of the United States.

**Claims based on traditional homeopathic practice, not accepted medical evidence. Not FDA evaluated.

INACTIVE INGREDIENTS: Purified Water, USP Ethanol Alcohol 20%

QUESTIONS AND COMMENTS?

Natural Creations, Inc. / Woodbine, IA 51579 / 712-647-1600

PURPOSE

USES: Temporarily relieves symptoms related to motion sickness.**

KEEP OUT OF REACH OF CHILDREN

KEEP OUT OF THE REACH OF CHILDREN. In case of overdose (or accidental ingestion) get medical help or contact a Poison Control Center.

PACKAGE LABEL

NDC: 43406-0099-1

MOTION SICKNESS HP

HOMEOPATHIC

1 fl oz (30 mL) / 20% Alcohol